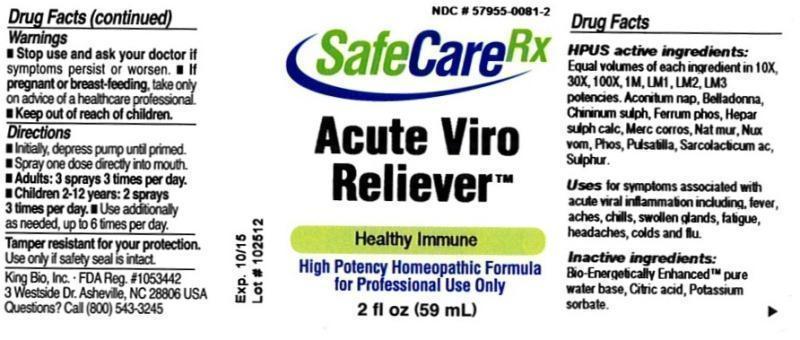 DRUG LABEL: Acute Viro Reliever
NDC: 57955-0081 | Form: LIQUID
Manufacturer: King Bio Inc.
Category: homeopathic | Type: HUMAN PRESCRIPTION DRUG LABEL
Date: 20121211

ACTIVE INGREDIENTS: ACONITUM NAPELLUS 10 [hp_X]/59 mL; ATROPA BELLADONNA 10 [hp_X]/59 mL; QUININE SULFATE 10 [hp_X]/59 mL; FERROSOFERRIC PHOSPHATE 10 [hp_X]/59 mL; CALCIUM SULFIDE 10 [hp_X]/59 mL; MERCURIC CHLORIDE 10 [hp_X]/59 mL; SODIUM CHLORIDE 10 [hp_X]/59 mL; STRYCHNOS NUX-VOMICA SEED 10 [hp_X]/59 mL; PHOSPHORUS 10 [hp_X]/59 mL; PULSATILLA VULGARIS 10 [hp_X]/59 mL; LACTIC ACID, L- 10 [hp_X]/59 mL; SULFUR 10 [hp_X]/59 mL
INACTIVE INGREDIENTS: WATER; CITRIC ACID MONOHYDRATE; POTASSIUM SORBATE

Acute Viro Reliever

Active Ingredients

HPUS active ingredients: Equal volumes of each ingredient in 10X, 30X, 100X, 1M, LM1, LM2, LM3 potencies.

Aconitum napellus, Belladonna, Chininum sulphuricum, Ferrum phosphoricum, Hepar sulphuris calcareum, Mercurius corrosivus, Natrum muriaticum, Nux vomica, Phosphorus, Pulsatilla, Sarcolacticum acidum, Sulphur

Purpose

Uses for symptoms associated with acute viral inflammation including:

- fever
- aches
- chills
- swollen glands
- fatigue
- headaches
- colds and flu

Inactive Ingredients

Bio-Energetically Enhanced pure water base, Citric acid and Potassium sorbate.

Warnings

Stop use and ask your doctor if symptoms persist or worsen. If pregnant or breast-feeding, take only on advice of a healthcare professional. Keep out of reach of children.

Tamper resistant for your protection.

Use only if safety seal is intact.

Keep out of reach of children.

Directions

- Initially, depress pump until primed.
- Spray one dose directly into mouth.
- Adults: 3 sprays 3 times per day
- Children 2-12 years: 2 sprays 3 times per day
- Use additionally as needed, up to 6 times per day.

Indications and Usage

Uses for symptoms associated with acute viral inflammation including fever, aches, chills, swollen glands, fatigue, headaches, colds and flu.

PACKAGE LABEL

King Bio Inc.

3 Westside Dr.

Asheville, NC 28806

Questions? Call (800) 543-3245